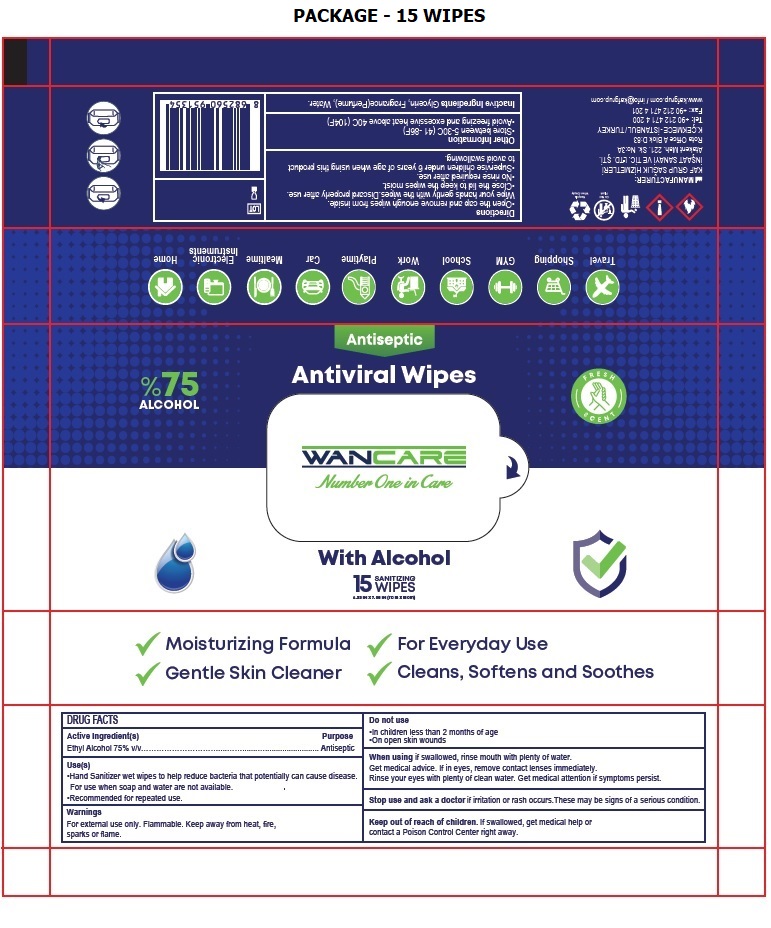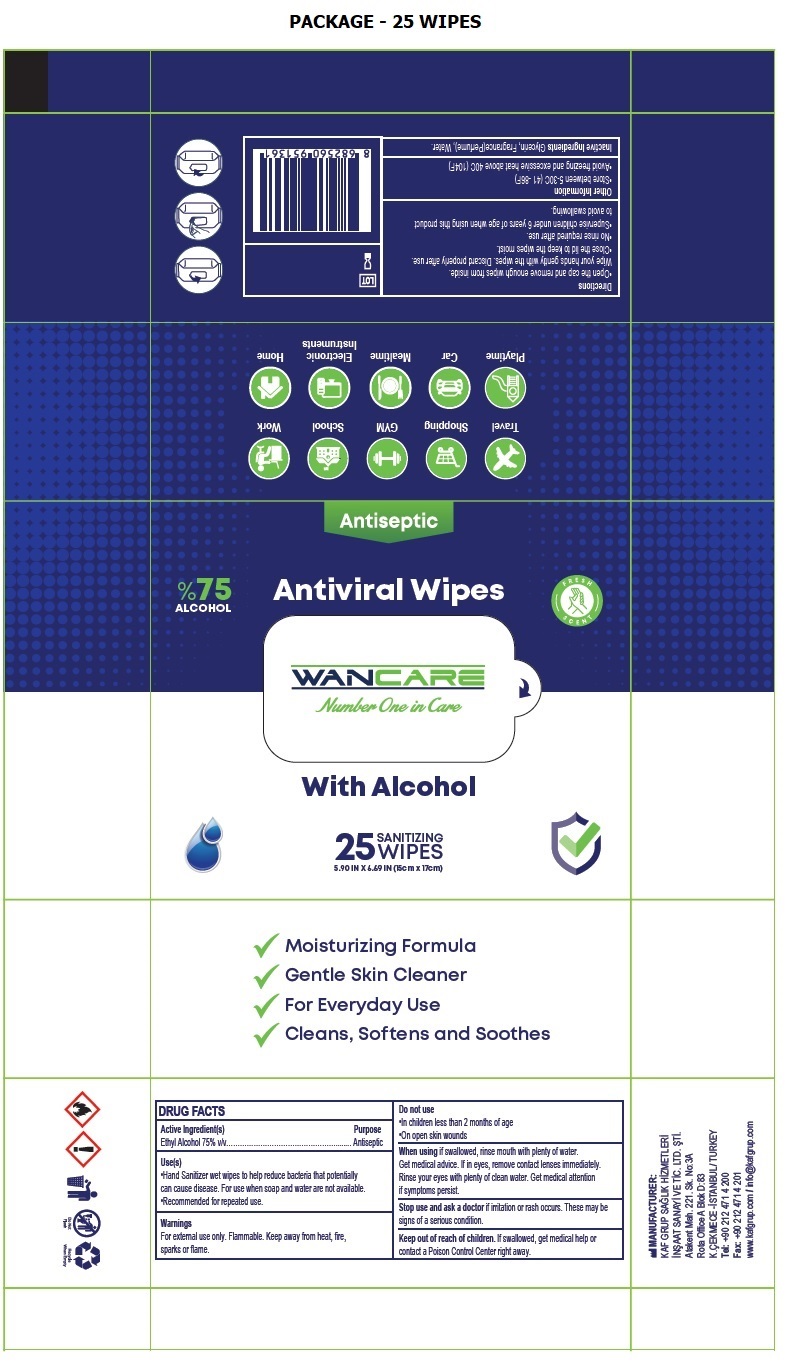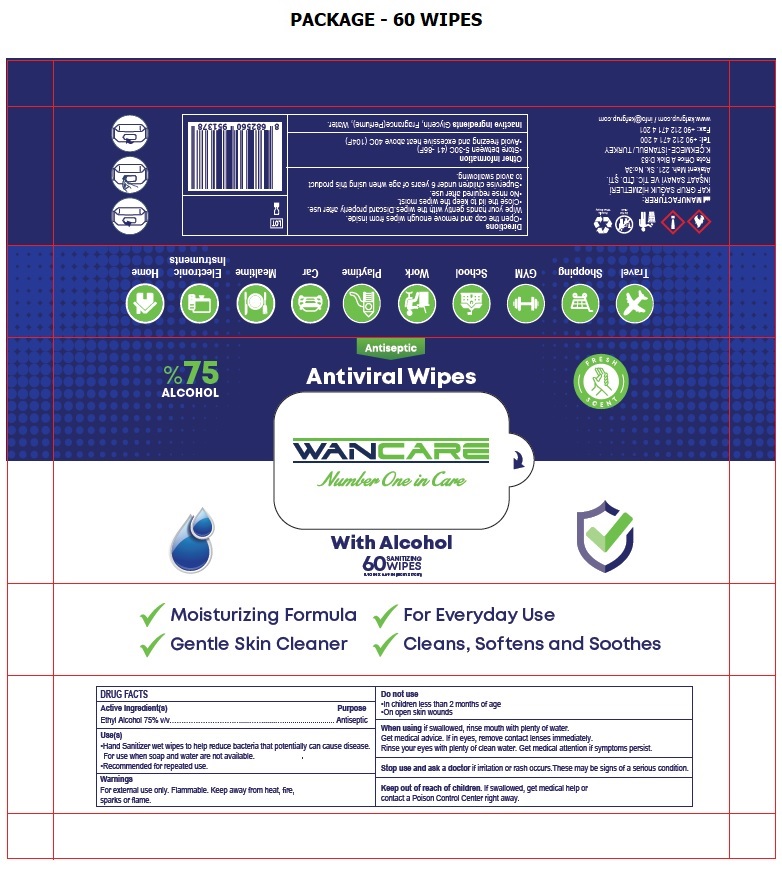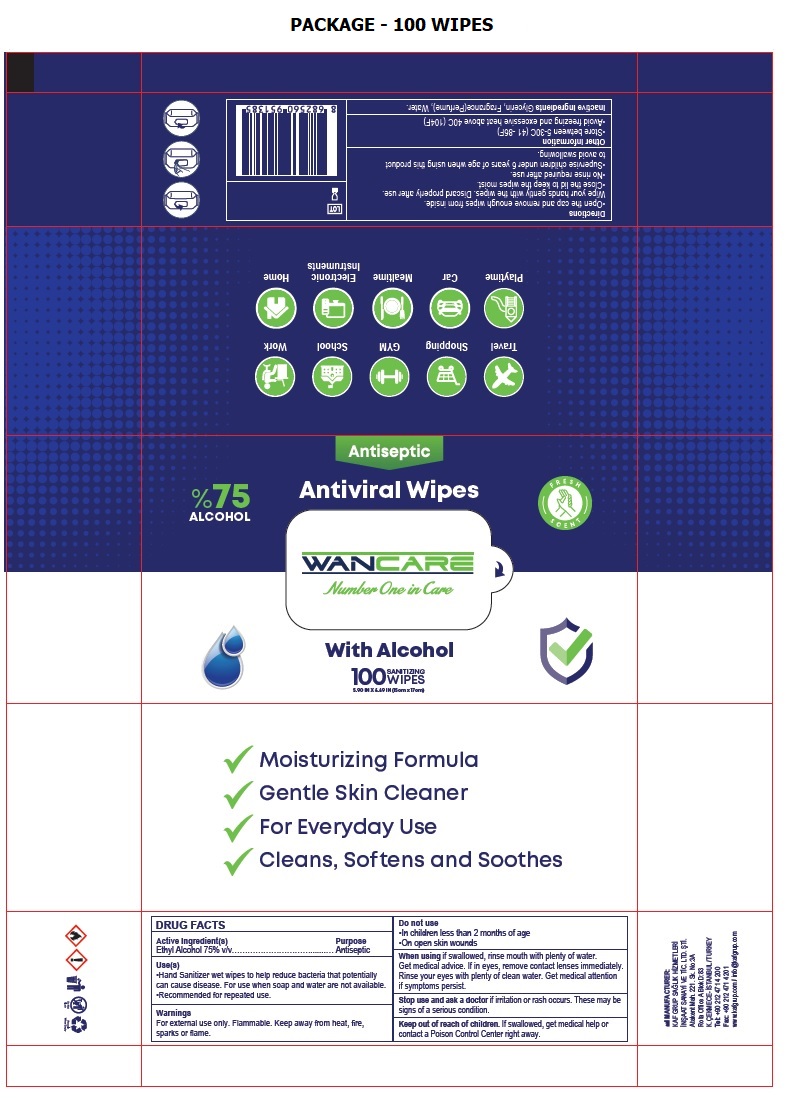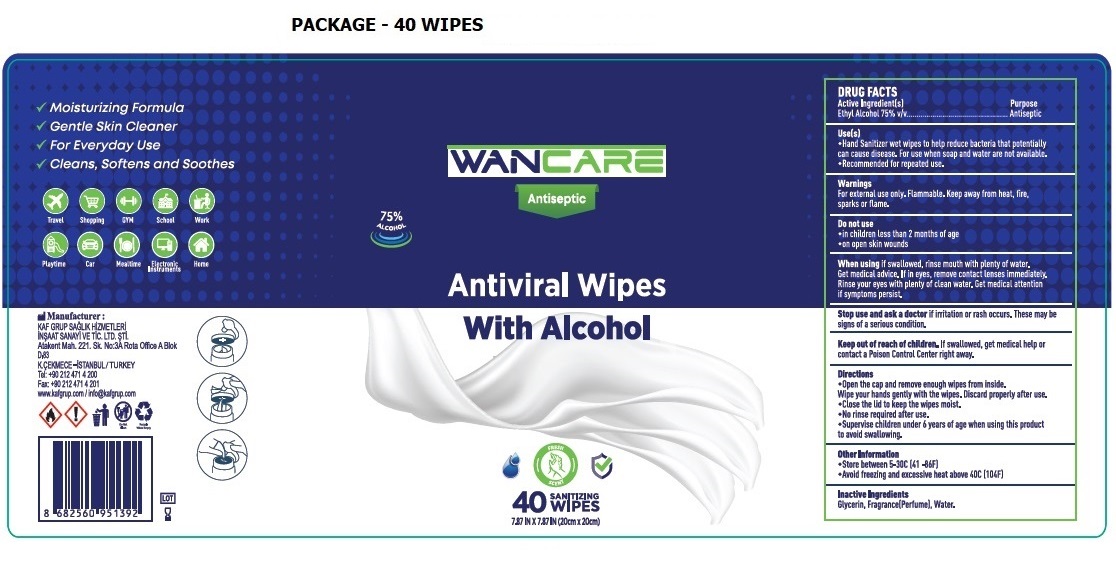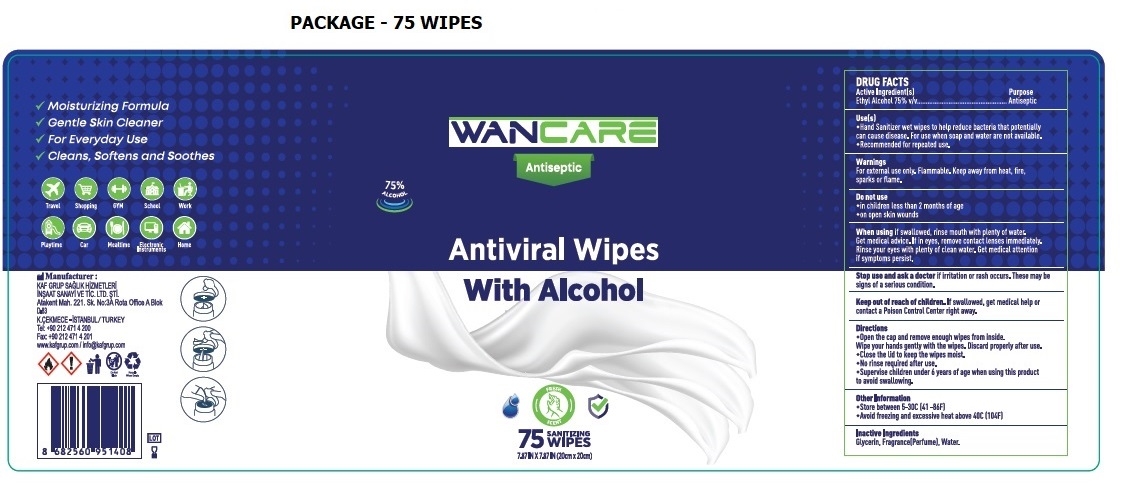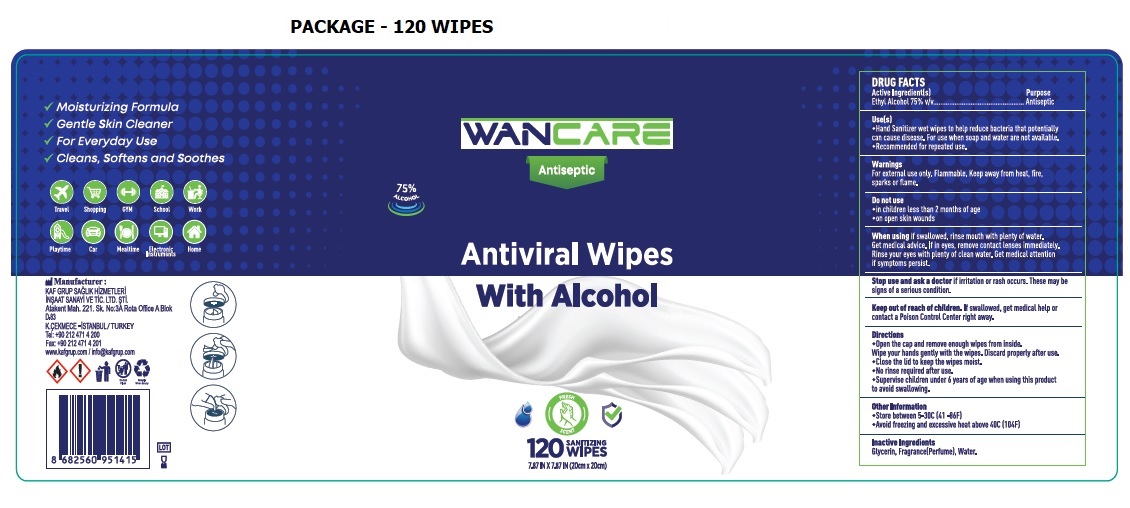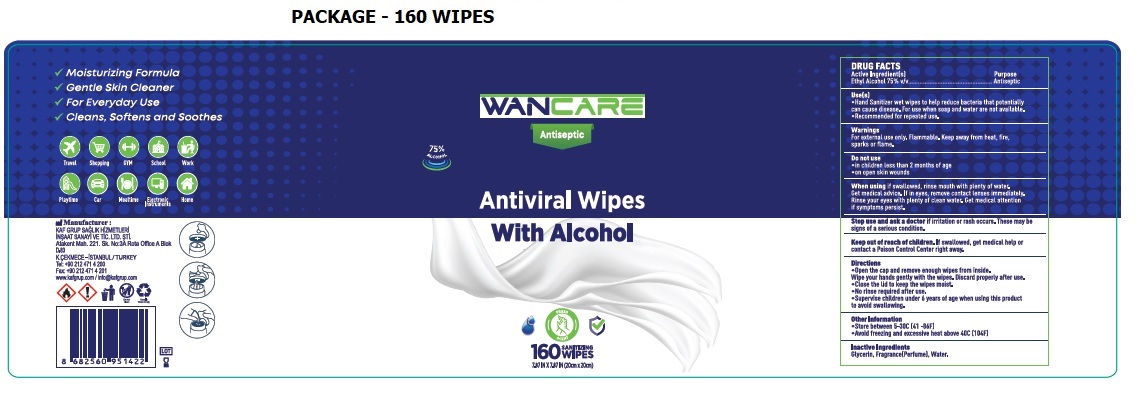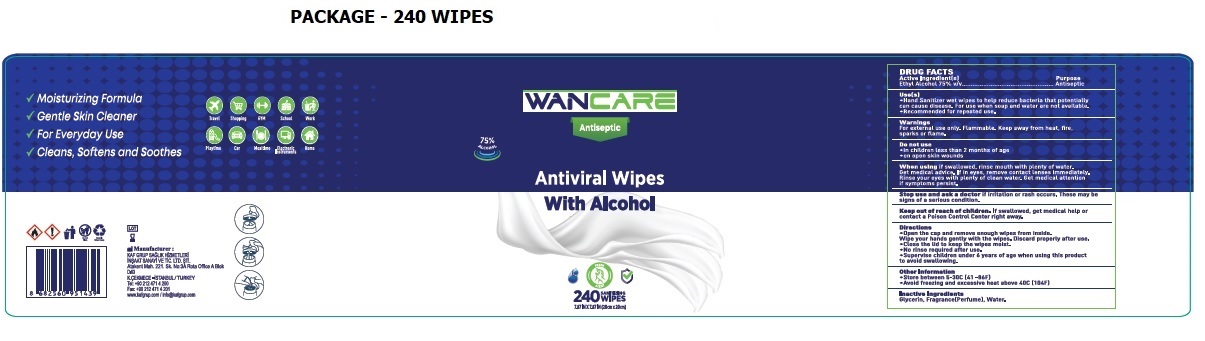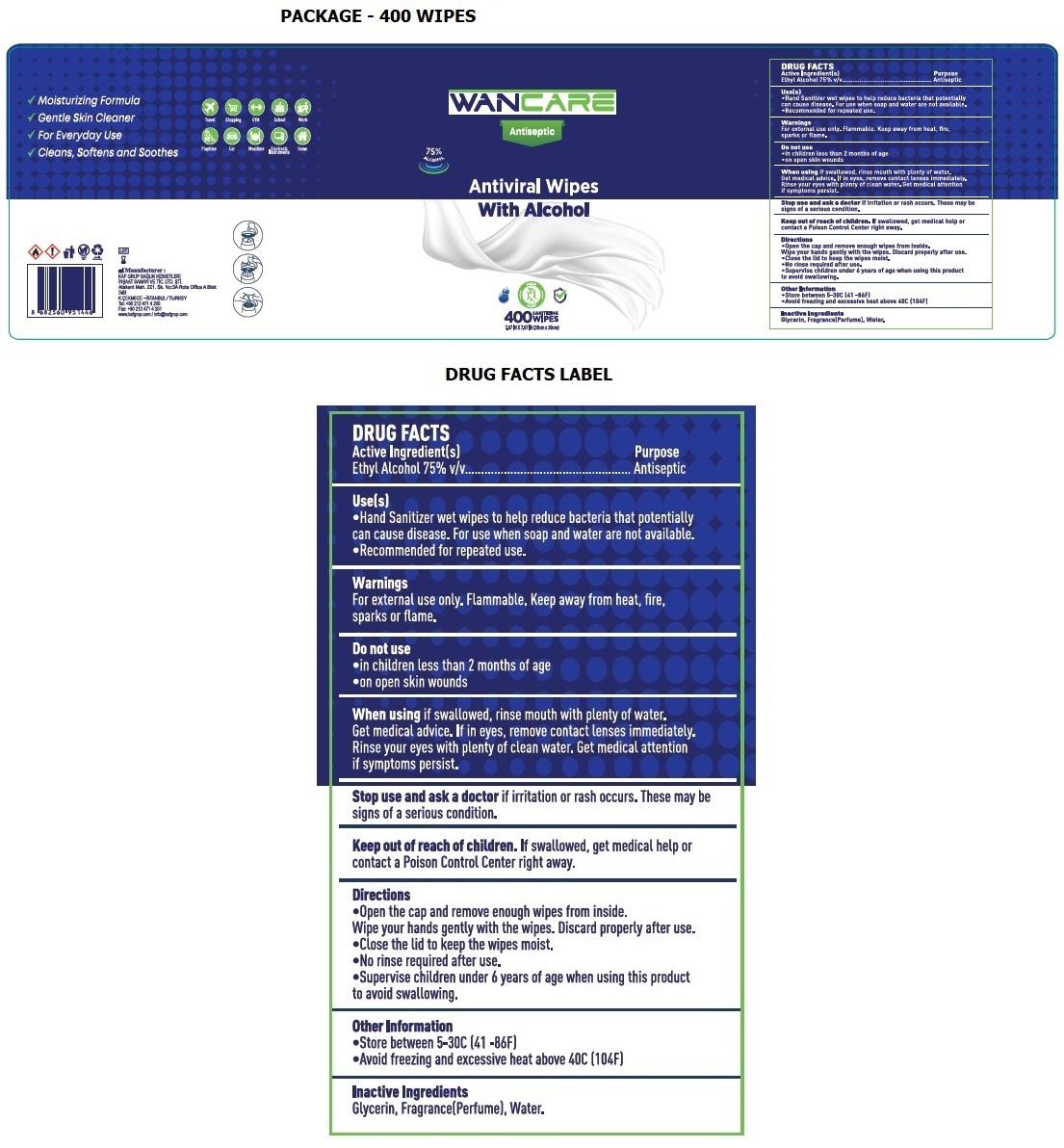 DRUG LABEL: WANCARE
NDC: 81314-302 | Form: CLOTH
Manufacturer: KAF GRUP SAGLIK HIZMETLERI INSAAT SANAYI VE TICARET LIMITED SIRKETI
Category: otc | Type: HUMAN OTC DRUG LABEL
Date: 20210108

ACTIVE INGREDIENTS: ALCOHOL 75 mL/100 mL
INACTIVE INGREDIENTS: GLYCERIN; WATER

WANCARE Antiviral Wipes With Alcohol

Active Ingredient(s)

Ethyl Alcohol 75% v/v

Purpose

Antiseptic

Use(s)

• Hand Sanitizer wet wipes to help reduce bacteria that potentially can cause disease. For use when soap and water are not available.

• Recommended for repeated use.

Warnings

For external use only.

Flammable. Keep away from heat, fire, sparks or flame.

Do not use

• in children less than 2 months of age
• on open skin wounds

When using if swallowed, rinse mouth with plenty of water.

Get medical advice, If in eyes, remove contact lenses immediately. Rinse your eyes with plenty of clean water. Get medical attention if symptoms persist.

Stop use and ask a doctor if irritation or rash occurs. These may be signs of a serious condition.

Keep out of reach of children. If swallowed, get medical help or contact a Poison Control Center right away.

Directions

• Open the cap and remove enough wipes from inside.

Wipe your hands gently with the wipes. Discard properly after use.

• Close the lid to keep the wipes moist.

• No rinse required after use.

• Supervise children under 6 years of age when using this product to avoid swallowing.

Other Information

• Store between 5-30C (41 -86F)

• Avoid freezing and excessive heat above 40C (104F)

Inactive Ingredients

Glycerin, Fragrance (Perfume), Water.

75% ALCOHOL

Number One in Care

FRESH SCENT

√ Moisturizing Formula

√ Gentle Skin Cleaner

√ For Everyday use

√ Cleans, Softens and Soothes

Travel Shopping GYM School Work

Playtime Car Mealtime Electronic Instruments Home

Manufacturer:

KAF GRUP SAGLIK HIZMETLERI

INSAAT SANAYI VE TIC. LTD. STI.

Atakent Mah. 221. Sk. No:3A Rota Office A Blok

D:83

K.CEKMECE -ISTANBUL/TURKEY

Tel: +90 212 471 4 200

Fax: +90 212 471 4 201

www.kafgrup.com / info@kafgrup.com

Do Not Flush

Recycle when Empty